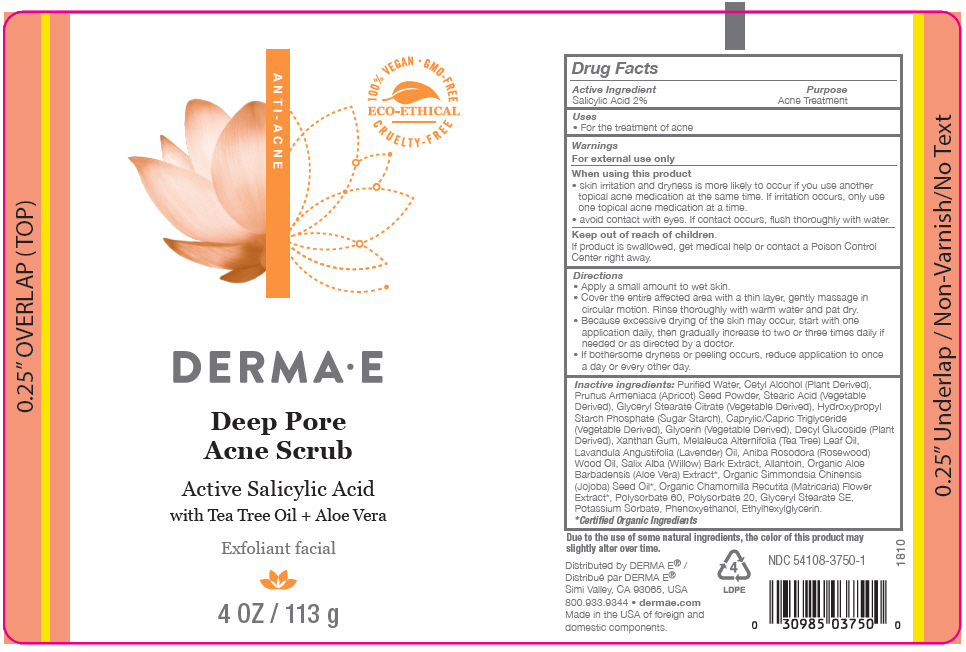 DRUG LABEL: Deep Pore Acne Scrub
NDC: 54108-3750 | Form: PASTE
Manufacturer: derma e
Category: otc | Type: HUMAN OTC DRUG LABEL
Date: 20181108

ACTIVE INGREDIENTS: SALICYLIC ACID 20 mg/1 g
INACTIVE INGREDIENTS: WATER; PRUNUS ARMENIACA SEED; CETYL ALCOHOL; GLYCERYL STEARATE CITRATE; HYDROXYPROPYL DISTARCH PHOSPHATE, HIGH AMYLOSE CORN; MEDIUM-CHAIN TRIGLYCERIDES; GLYCERIN; STEARIC ACID; DECYL GLUCOSIDE; TEA TREE OIL; LAVENDER OIL; ALLANTOIN; SALIX ALBA BARK; ROSEWOOD OIL; JOJOBA OIL; MATRICARIA CHAMOMILLA WHOLE; ALOE VERA LEAF; XANTHAN GUM; POLYSORBATE 20; POLYSORBATE 60; GLYCERYL STEARATE SE; POTASSIUM SORBATE; PHENOXYETHANOL; ETHYLHEXYLGLYCERIN

Deep Pore Acne Scrub

Drug Facts

Active Ingredient

Salicylic Acid 2%

Purpose

Acne Treatment

Uses

- For the treatment of acne

Warnings

For external use only

When using this product

- skin irritation and dryness is more likely to occur if you use another topical acne medication at the same time. If irritation occurs, only use one topical acne medication at a time.
- avoid contact with eyes. If contact occurs, flush thoroughly with water.

Keep out of reach of children.

If product is swallowed, get medical help or contact a Poison Control Center right away.

Directions

- Apply a small amount to wet skin.
- Cover the entire affected area with a thin layer, gently massage in circular motion. Rinse thoroughly with warm water and pat dry.
- Because excessive drying of the skin may occur, start with one application daily, then gradually increase to two or three times daily if needed or as directed by a doctor.
- If bothersome dryness or peeling occurs, reduce application to once a day or every other day.

Inactive ingredients

Purified Water, Cetyl Alcohol (Plant Derived), Prunus Armeniaca (Apricot) Seed Powder, Stearic Acid (Vegetable Derived), Glyceryl Stearate Citrate (Vegetable Derived), Hydroxypropyl Starch Phosphate (Sugar Starch), Caprylic/Capric Triglyceride (Vegetable Derived), Glycerin (Vegetable Derived), Decyl Glucoside (Plant Derived), Xanthan Gum, Melaleuca Alternifolia (Tea Tree) Leaf Oil, Lavandula Angustifolia (Lavender) Oil, Aniba Rosodora (Rosewood) Wood Oil, Salix Alba (Willow) Bark Extract, Allantoin, Organic Aloe Barbadensis (Aloe Vera) Extract [Certified Organic Ingredients] , Organic Simmondsia Chinensis (Jojoba) Seed Oil, Organic Chamomilla Recutita (Matricaria) Flower Extract, Polysorbate 60, Polysorbate 20, Glyceryl Stearate SE, Potassium Sorbate, Phenoxyethanol, Ethylhexylglycerin.

Distributed by DERMA E®
Simi Valley, CA 93065, USA

PRINCIPAL DISPLAY PANEL - 113 g Tube Label

ANTI-ACNE

100% VEGAN • GMO-FREE
ECO-ETHICAL
CRUELTY-FREE

DERMA•E

Deep Pore
Acne Scrub

Active Salicylic Acid
with Tea Tree Oil + Aloe Vera

4 OZ / 113 g